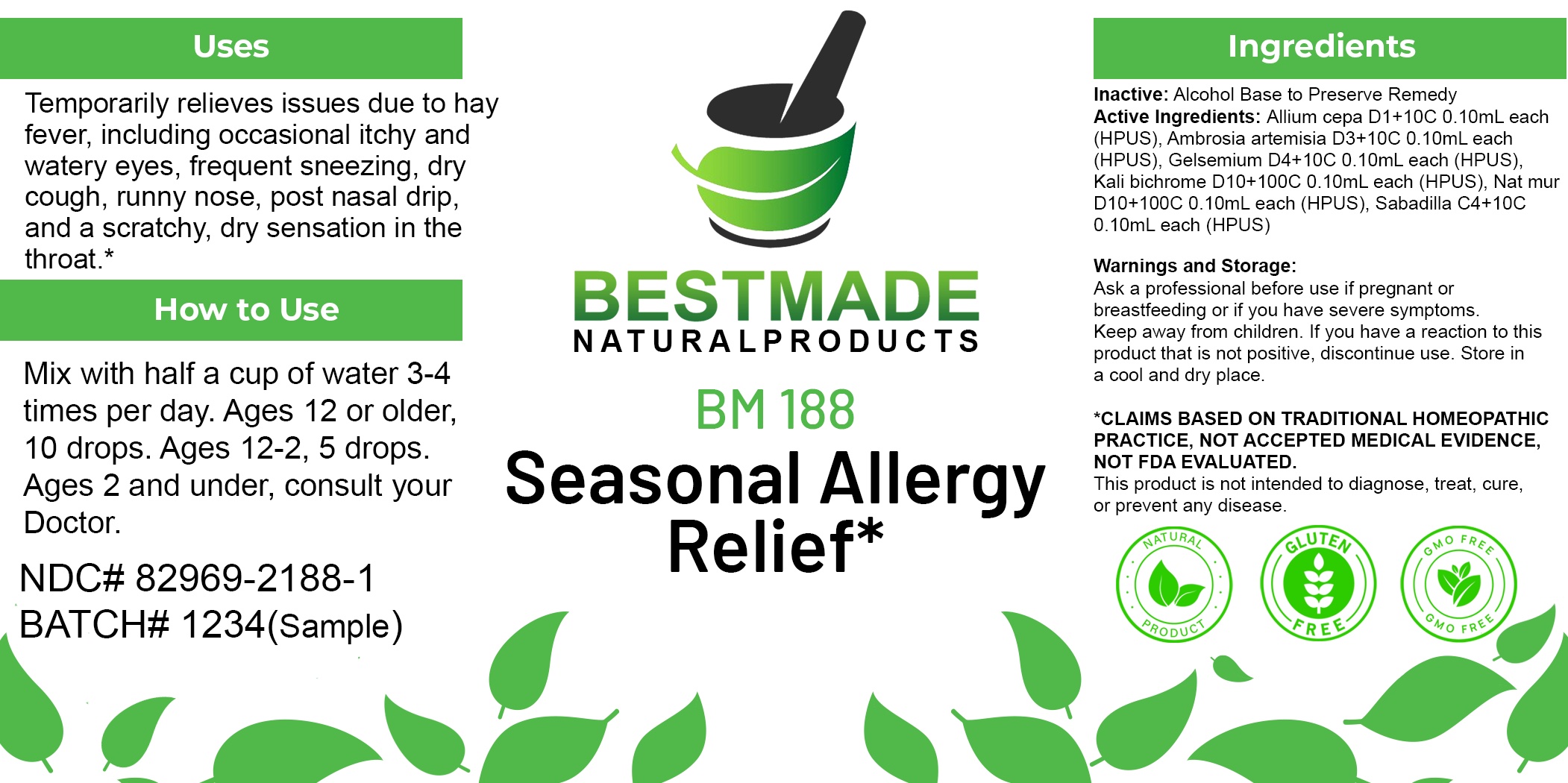 DRUG LABEL: Bestmade Natural Products BM188
NDC: 82969-2188 | Form: LIQUID
Manufacturer: Bestmade Natural Products
Category: homeopathic | Type: HUMAN OTC DRUG LABEL
Date: 20250220

ACTIVE INGREDIENTS: ONION 30 [hp_C]/30 [hp_C]; POTASSIUM DICHROMATE 30 [hp_C]/30 [hp_C]; SCHOENOCAULON OFFICINALE SEED 30 [hp_C]/30 [hp_C]; AMBROSIA ARTEMISIIFOLIA 30 [hp_C]/30 [hp_C]; SODIUM CHLORIDE 30 [hp_C]/30 [hp_C]; GELSEMIUM SEMPERVIRENS ROOT 30 [hp_C]/30 [hp_C]
INACTIVE INGREDIENTS: ALCOHOL 30 [hp_C]/30 [hp_C]

BM188

DOSAGE AND ADMINISTRATION

How to Use

Mix with half a cup of water 3-4 times per day. Ages 12 or older, 10 drops. Ages 12-2, 5 drops. Ages 2 and under, consult your Doctor.

Inactive:

Alcohol Base to Preserve Product

ACTIVE INGREDIENT

Active Ingredients: Allium cepa D1+10C 0.10mL each (HPUS), Ambrosia artemisia D3+10C 0.10mL each (HPUS), Gelsemium D4+10C 0.10mL each (HPUS), Kali bichrome D10+100C 0.10mL each (HPUS), Nat mur D10+100C 0.10mL each (HPUS), Sabadilla C4+10C 0.10mL each (HPUS)

KEEP OUT OF REACH OF CHILDREN

Warnings and Storage:

Ask a professional before use if pregnant or breastfeeding or if you have severe symptoms.

Keep away from children. If you have a reaction to this product that is not positive, discontinue use. Store in a cool and dry place

*CLAIMS BASED ON TRADITIONAL HOMEOPATHIC PRACTICE, NOT ACCEPTED MEDICAL EVIDENCE NOT FDA EVALUATED.
This product is not intended to diagnose, treat, cure, or prevent any disease.

Warnings and Storage:

Ask a professional before use if pregnant or breastfeeding or if you have severe symptoms.

Keep away from children. If you have a reaction to this product that is not positive, discontinue use. Store in a cool and dry place

*CLAIMS BASED ON TRADITIONAL HOMEOPATHIC PRACTICE, NOT ACCEPTED MEDICAL EVIDENCE NOT FDA EVALUATED.
This product is not intended to diagnose, treat, cure, or prevent any disease.

Uses
Temporarily relieves issues due to hay fever, including occasional itchy and watery eyes, frequent sneezing, dry cough, runny nose, post nasal drip, and a scratchy, dry sensation in the throat *

Uses
Temporarily relieves issues due to hay fever, including occasional itchy and watery eyes, frequent sneezing, dry cough, runny nose, post nasal drip, and a scratchy, dry sensation in the throat *

Entire package label